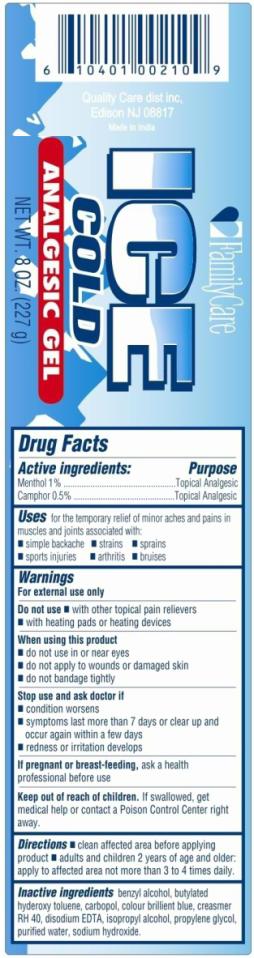 DRUG LABEL: Hot Ice Soothing Analgesic
NDC: 52271-159 | Form: GEL
Manufacturer: Quality Care Distributors LLC
Category: otc | Type: HUMAN OTC DRUG LABEL
Date: 20100731

ACTIVE INGREDIENTS: MENTHOL 2.27 g/227 g; CAMPHOR (SYNTHETIC) 1.14 g/227 g
INACTIVE INGREDIENTS: BENZYL ALCOHOL; BUTYLATED HYDROXYTOLUENE; CAMPHOR (SYNTHETIC); CARBOMER 934; EDETATE DISODIUM; ISOPROPYL ALCOHOL; PROPYLENE GLYCOL; SODIUM HYDROXIDE; WATER

Ice Cold Analgesic Gel

Drug Facts

Active Ingredients

Menthol 1%

Camphor 0.5%

Purpose

Topical analgesic

Uses

for the temporary relief of minor aches and pains in muscles and joins associated with

- simple backache
- strains
- sprains
- sports injuries
- arthritis
- bruises

Warnings

For external use only.

Do not use

- with other topical pain relievers
- with heating pads or heating devices

When using this product

- do not use in or near eyes
- do not apply to wounds or damaged skin
- do not bandage tightly

Stop use and ask doctor if

- condition worsen
- symptoms last more than 7 days or clear up and occurs again with a few days
- redness or irritation develops

If pregnant or breast –feeding, ask a health professional before use

Keep out of reach of children.

If swallowed, get medical help or contact a Poison Control Center right way.

Directions

- clean affected area before applying product
- adults and children 2 years of age and older: apply to affected area not more than 3 to 4 times daily.

Inactive ingredients

Benzyl alcohol, butylated hyderoxy toluene, carbopol, colour brilliant blue, creasmer RH 40, disodium Edta, isopropyl alcohol, propylene glycol, purified water, sodium hydroxide

Principal Display Panel

FamilyCare
ICE
COLD
ANALGESIC GEL
NET WT. 8 OZ. (227 g)